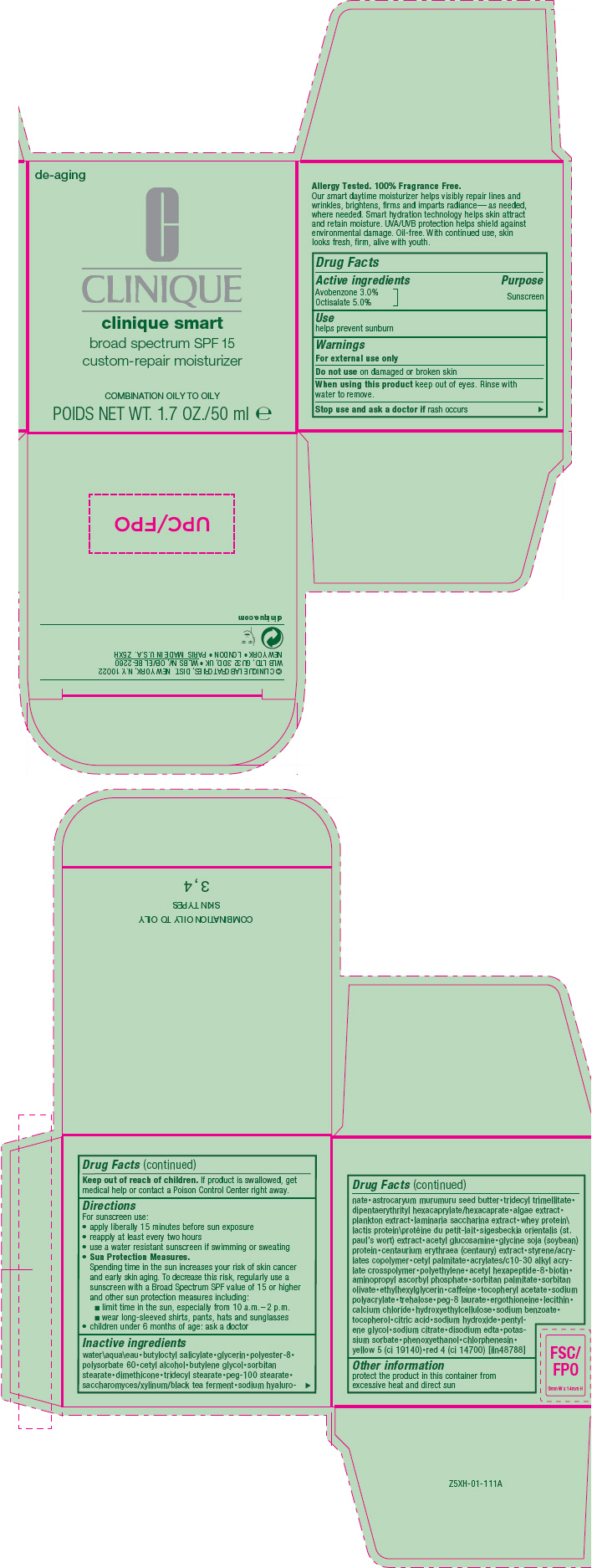 DRUG LABEL: CLINIQUE  SMART CUSTOM REPAIR MOISTURIZER BROAD SPECTRUM SPF 15 - COMBINATION/OILY TO OILY
NDC: 49527-050 | Form: CREAM
Manufacturer: CLINIQUE LABORATORIES LLC
Category: otc | Type: HUMAN OTC DRUG LABEL
Date: 20231005

ACTIVE INGREDIENTS: AVOBENZONE 30 mg/1 mL; OCTISALATE 50 mg/1 mL
INACTIVE INGREDIENTS: POLYSORBATE 60; GLYCERIN; CETYL ALCOHOL; BUTYLENE GLYCOL; SORBITAN MONOSTEARATE; DIMETHICONE; TRIDECYL STEARATE; PEG-100 STEARATE; HYALURONATE SODIUM; ASTROCARYUM MURUMURU SEED BUTTER; TRIDECYL TRIMELLITATE; DIPENTAERYTHRITYL HEXACAPRYLATE/HEXACAPRATE; AGAR, UNSPECIFIED; TAMARIND SEED; N-ACETYLGLUCOSAMINE; SOY PROTEIN; CENTAURIUM ERYTHRAEA; CETYL PALMITATE; HIGH DENSITY POLYETHYLENE; ACETYL HEXAPEPTIDE-8; BIOTIN; AMINOPROPYL ASCORBYL PHOSPHATE; SORBITAN MONOPALMITATE; SORBITAN OLIVATE; ETHYLHEXYLGLYCERIN; CAFFEINE; .ALPHA.-TOCOPHEROL ACETATE; TREHALOSE; ERGOTHIONEINE; SODIUM BENZOATE; SODIUM HYDROXIDE; PENTYLENE GLYCOL; EDETATE DISODIUM; PHENOXYETHANOL; CHLORPHENESIN; FD&C YELLOW NO. 5; FD&C RED NO. 4; POTASSIUM SORBATE; SODIUM CITRATE, UNSPECIFIED FORM; CITRIC ACID ACETATE; TOCOPHEROL; HYDROXYETHYL CELLULOSE (100 MPA.S AT 2%); CALCIUM CHLORIDE; LECITHIN, SOYBEAN; PEG-8 LAURATE; SODIUM POLYACRYLATE (2500000 MW); CARBOMER INTERPOLYMER TYPE A (ALLYL SUCROSE CROSSLINKED); BUTYL ACRYLATE/METHYL METHACRYLATE/METHACRYLIC ACID COPOLYMER (18000 MW); SIGESBECKIA ORIENTALIS FLOWERING TOP; WHEY; SACCHARINA LATISSIMA; WATER; BUTYLOCTYL SALICYLATE

CLINIQUE SMART CUSTOM REPAIR MOISTURIZER BROAD SPECTRUM SPF 15 - COMBINATION/OILY TO OILY

Drug Facts

Active ingredients

Avobenzone 3%
Octisalate 5%

Purpose

Sunscreen

Use

helps prevent sunburn

Warnings

For external use only

Do not use on damaged or broken skin

When using this product keep out of eyes. Rinse with water to remove.

Stop use and ask a doctor if rash occurs

Keep out of reach of children. If product is swallowed, get medical help or contact a Poison Control Center right away.

Directions

For sunscreen use:

- apply liberally 15 minutes before sun exposure
- reapply at least every two hours
- use a water resistant sunscreen if swimming or sweating
- Sun Protection Measures.
  Spending time in the sun increases your risk of skin cancer and early skin aging. To decrease this risk, regularly use a sunscreen with a Broad Spectrum SPF value of 15 or higher and other sun protection measures including:
  - limit time in the sun, especially from 10 a.m.–2 p.m.
  - wear long-sleeved shirts, pants, hats and sunglasses
- children under 6 months of age: ask a doctor

Inactive ingredients

water\aqua\eau•butyloctyl salicylate•glycerin•polyester-8• polysorbate 60•cetyl alcohol•butylene glycol•sorbitan stearate•dimethicone•tridecyl stearate•peg-100 stearate• saccharomyces/xylinum/black tea ferment•sodium hyaluro-nate•astrocaryum murumuru seed butter•tridecyl trimellitate• dipentaerythrityl hexacaprylate/hexacaprate•algae extract• plankton extract•laminaria saccharina extract•whey protein\lactis protein\protéine du petit-lait•sigesbeckia orientalis (st. paul's wort) extract•acetyl glucosamine•glycine soja (soybean) protein•centaurium erythraea (centaury) extract•styrene/acrylates copolymer•cetyl palmitate•acrylates/c10-30 alkyl acrylate crosspolymer•polyethylene•acetyl hexapeptide-8•biotin• aminopropyl ascorbyl phosphate•sorbitan palmitate•sorbitan olivate•ethylhexylglycerin•caffeine•tocopheryl acetate•sodium polyacrylate•trehalose•peg-8 laurate•ergothioneine•lecithin• calcium chloride•hydroxyethylcellulose•sodium benzoate• tocopherol•citric acid•sodium hydroxide•pentylene glycol•sodium citrate•disodium edta•potassium sorbate•phenoxyethanol•chlorphenesin• yellow 5 (ci 19140)•red 4 (ci 14700) [iln48788]

Other information

protect the product in this container from excessive heat and direct sun

PRINCIPAL DISPLAY PANEL - 50 ml Jar Carton

de-aging

CLINIQUE

clinique smart
broad spectrum SPF 15
custom-repair moisturizer

COMBINATION OILY TO OILY

NET WT. 1.7 OZ./50 ml e